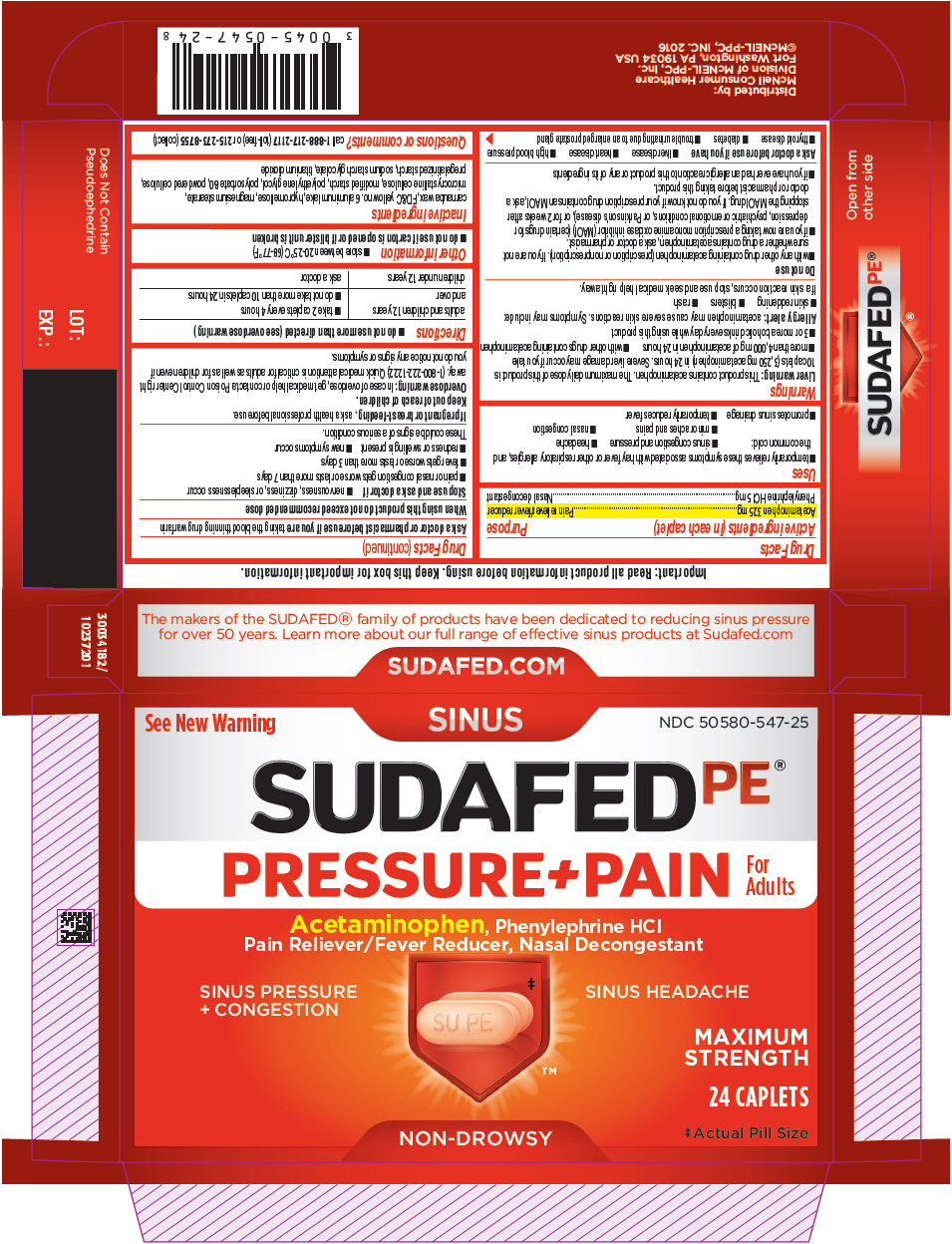 DRUG LABEL: SUDAFED PE Pressure Plus Pain
NDC: 50580-547 | Form: TABLET, FILM COATED
Manufacturer: Kenvue Brands LLC
Category: otc | Type: HUMAN OTC DRUG LABEL
Date: 20241108

ACTIVE INGREDIENTS: ACETAMINOPHEN 325 mg/1 1; PHENYLEPHRINE HYDROCHLORIDE 5 mg/1 1
INACTIVE INGREDIENTS: CARNAUBA WAX; FD&C YELLOW NO. 6; ALUMINUM OXIDE; HYPROMELLOSE, UNSPECIFIED; MAGNESIUM STEARATE; MICROCRYSTALLINE CELLULOSE; POLYETHYLENE GLYCOL, UNSPECIFIED; POLYSORBATE 80; POWDERED CELLULOSE; SODIUM STARCH GLYCOLATE TYPE A; TITANIUM DIOXIDE

SUDAFED PE® Pressure+Pain

Drug Facts

ACTIVE INGREDIENT

Active ingredients (in each caplet) | Purpose
Acetaminophen 325 mg | Pain reliever/fever reducer
Phenylephrine HCl 5 mg | Nasal decongestant

Uses

- temporarily relieves these symptoms associated with hay fever or other respiratory allergies, and the common cold:
  - sinus congestion and pressure
  - headache
  - minor aches and pains
  - nasal congestion
- promotes sinus drainage
- temporarily reduces fever

Warnings

Liver warning

This product contains acetaminophen. The maximum daily dose of this product is 10 caplets (3,250 mg acetaminophen) in 24 hours. Severe liver damage may occur if you take

- more than 4,000 mg of acetaminophen in 24 hours
- with other drugs containing acetaminophen
- 3 or more alcoholic drinks every day while using this product

Allergy alert: acetaminophen may cause severe skin reactions. Symptoms may include:

- skin reddening
- blisters
- rash

If a skin reaction occurs, stop use and seek medical help right away.

Do not use

- with any other drug containing acetaminophen (prescription or nonprescription). If you are not sure whether a drug contains acetaminophen, ask a doctor or pharmacist.
- if you are now taking a prescription monoamine oxidase inhibitor (MAOI) (certain drugs for depression, psychiatric or emotional conditions, or Parkinson's disease), or for 2 weeks after stopping the MAOI drug. If you do not know if your prescription drug contains an MAOI, ask a doctor or pharmacist before taking this product.
- if you have ever had an allergic reaction to this product or any of its ingredients

Ask a doctor before use if you have

- liver disease
- heart disease
- high blood pressure
- thyroid disease
- diabetes
- trouble urinating due to an enlarged prostate gland

Ask a doctor or pharmacist before use if you are taking the blood thinning drug warfarin

When using this product do not exceed recommended dose

Stop use and ask a doctor if

- nervousness, dizziness, or sleeplessness occur
- pain or nasal congestion gets worse or lasts more than 7 days
- fever gets worse or lasts more than 3 days
- redness or swelling is present
- new symptoms occur

These could be signs of a serious condition.

PREGNANCY OR BREAST FEEDING

If pregnant or breast-feeding, ask a health professional before use.

Keep out of reach of children.

Overdose warning

In case of overdose, get medical help or contact a Poison Control Center right away. (1-800-222-1222) Quick medical attention is critical for adults as well as for children even if you do not notice any signs or symptoms.

Directions

- do not use more than directed (see overdose warning)

adults and children 12 years and over | - take 2 caplets every 4 hours - do not take more than 10 caplets in 24 hours
children under 12 years | ask a doctor

Other information

- store between 20-25°C (68-77°F)
- do not use if carton is opened or if blister unit is broken

Inactive ingredients

carnauba wax, FD&C yellow no. 6 aluminum lake, hypromellose, magnesium stearate, microcrystalline cellulose, modified starch, polyethylene glycol, polysorbate 80, powdered cellulose, pregelatinized starch, sodium starch glycolate, titanium dioxide

Questions or comments?

call 1-888-217-2117 (toll-free) or 215-273-8755 (collect)

PRINCIPAL DISPLAY PANEL

See New Warning

SINUS

NDC 50580-547-25

SUDAFEDPE®
PRESSURE +PAIN
For
Adults

Acetaminophen, Phenylephrine HCl
Pain Reliever/Fever Reducer, Nasal Decongestant

SINUS PRESSURE
+ CONGESTION

SINUS HEADACHE

MAXIMUM
STRENGTH

24 CAPLETS

NON-DROWSY

‡ Actual Pill Size